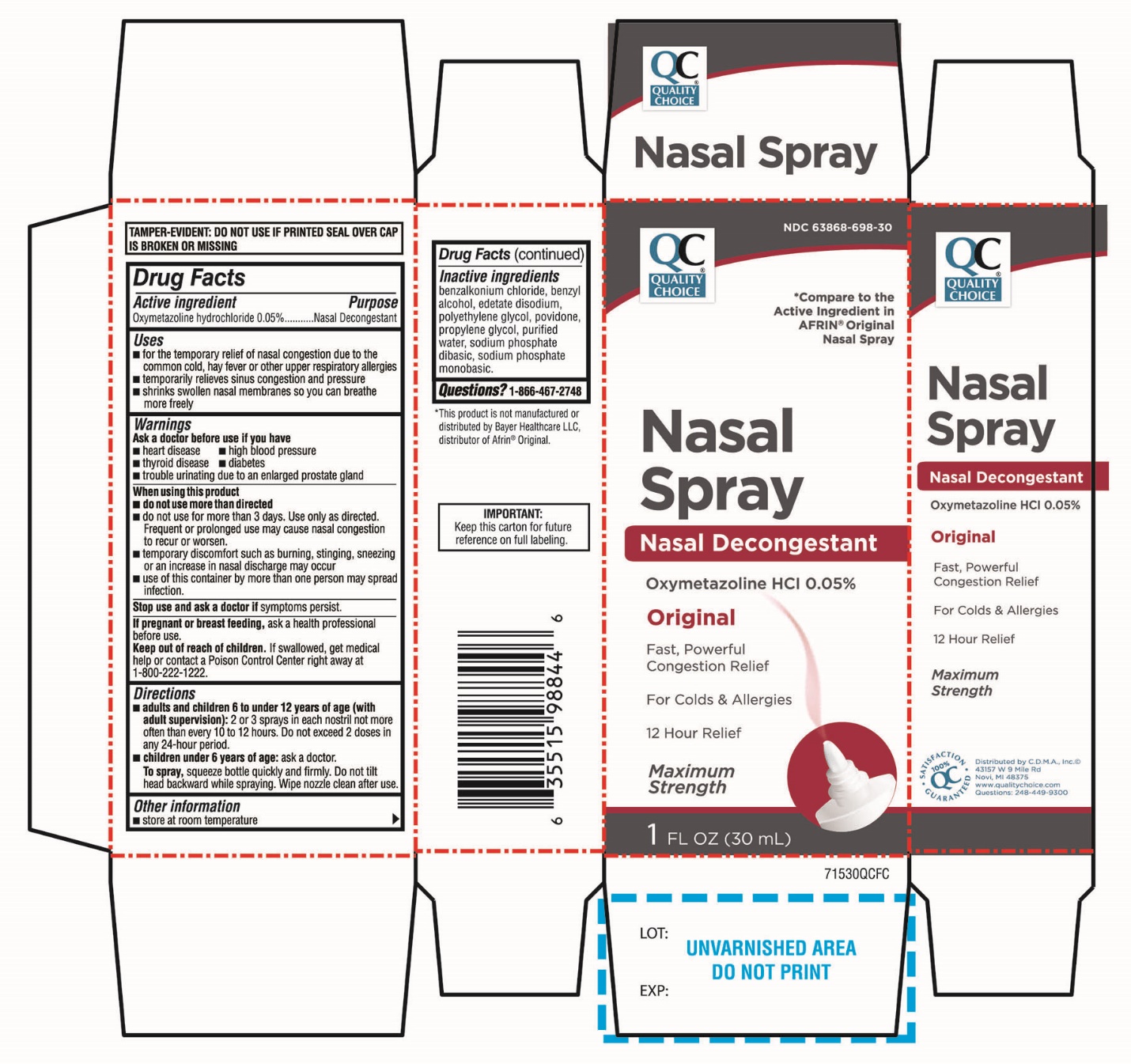 DRUG LABEL: Quality Choice

NDC: 63868-698 | Form: SPRAY
Manufacturer: CHAIN DRUG MARKETING ASSOCIATION
Category: otc | Type: HUMAN OTC DRUG LABEL
Date: 20251204

ACTIVE INGREDIENTS: OXYMETAZOLINE HYDROCHLORIDE 0.05 g/100 mL
INACTIVE INGREDIENTS: BENZALKONIUM CHLORIDE; BENZYL ALCOHOL; EDETATE DISODIUM; POLYETHYLENE GLYCOL, UNSPECIFIED; POVIDONE, UNSPECIFIED; PROPYLENE GLYCOL; WATER; SODIUM PHOSPHATE, DIBASIC, UNSPECIFIED FORM; SODIUM PHOSPHATE, MONOBASIC, UNSPECIFIED FORM

Quality Choice Nasal Oxymetazoline Spray Drug Facts

Active ingredient

Oxymetazoline hydrochloride 0.05%

Purpose

Nasal Decongestant

Uses

- temporarily relief of nasal congestion due to the ,common cold, hay fever or other upper respiratory allergies
- temporarily relieves sinus congestion and pressure
- shrinks swollen nasal membranes so you can breathe more freely

Ask a doctor before use if you have

- heart disease
- high blood pressure
- diabetes
- thyroid disease
- trouble urinating due to an enlarged prostate gland

When using this product

- do not use more than directed
- do not use for more than 3 days. Use only as directed. Frequent or prolonged use may cause nasal congestion to recur or worsen.
- temporary discomfort such as burning, stinging, sneezing or an increase in nasal discharge may occur
- use of this container by more than one person may spread infection

Stop use and ask a doctor if

symptoms persist

If pregnant or breast-feeding,

ask a health professional before use.

Keep out of reach of children.

If swallowed, get medical help or contact a Poison Control Center right away (1-800-222-1222).

Directions

- adults and children 6 to under 12 years of age (with adult supervision):2 or 3 sprays in each nostril not more often than every 10 to 12 hours. Do not exceed 2 doses in any 24-hour period.
- children under 6 years of age:ask a doctor

To Spray:squeeze bottle quickly and firmly. Do not tilt head backward while spraying. Wipe nozzle clean after use. Secure cap after use.

Other information

- store at room temperature

Inactive ingredients

benzalkonium chloride, benzyl alcohol, edetate disodium, polyethylene glycol, povidone, propylene glycol, purified water, sodium phosphate dibasic, sodium phosphate monobasic.

Questions or comments?

1-866-467-2748

Principal Display Panel

QUALITY CHOICE

NDC# 63868-698-30

*Compare to the Active Ingredient in AFRIN® Original Nasal Spray

Nasal Spray

Oxymetazoline HCl 0.05%

Nasal Decongestant

Original

Fast, Powerful Congestion Relief

For Colds & Allergies

12 Hour

Maximum Strength

1 FL OZ (30 mL)

100% QC SATISFACTION GURANTEED

Distributed by C.D.M.A., Inc.©

43157 W 9 Mile Rd

Novi, MI 48375

www.qualitychoice.com

Questions: 248-449-9300

*This product is not manufactured or distributed by Bayer Healthcare LLC, distributer of Afrin®Original.